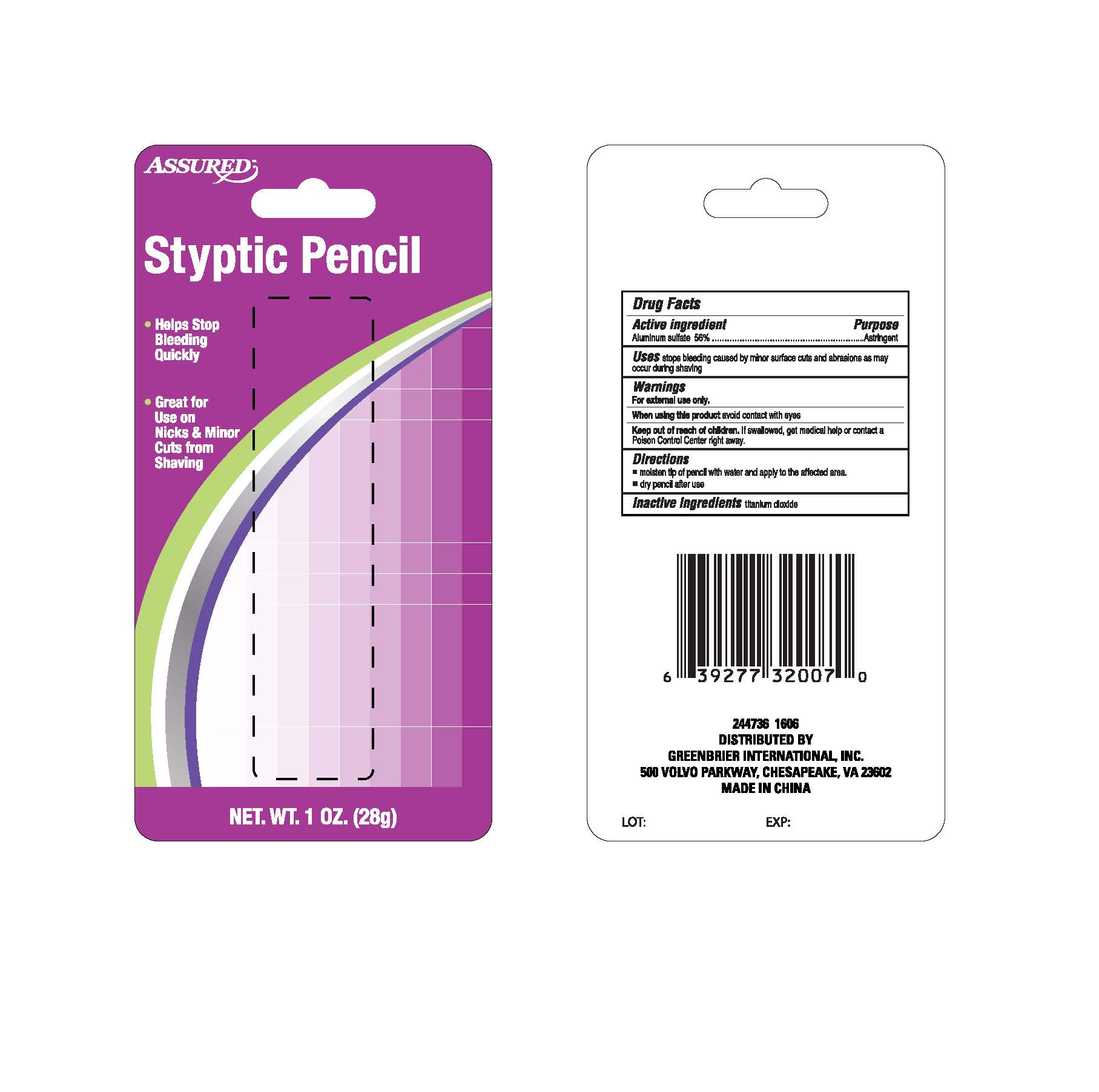 DRUG LABEL: Assured
NDC: 33992-0828 | Form: POWDER
Manufacturer: Greenbrier International
Category: otc | Type: HUMAN OTC DRUG LABEL
Date: 20160425

ACTIVE INGREDIENTS: ALUMINUM SULFATE 56 g/100 g
INACTIVE INGREDIENTS: TITANIUM DIOXIDE

Active ingredient

Aluminum sulfate 56%

Purpose

Astringent

INDICATIONS AND USAGE

Uses stops bleeding caused by minor surface cuts and abrasions as may

occur during shaving

Warnings

For external use only.

When using this product, avoid contact with eyes.

Keep out of reach of children. If swallowed, get medical help or contact a

Poison Control Centerright away.

Directions

- moisten tip of pencil with water and apply to affected area.
- dry pencil after use.

Inactive ingredients titanium dioxide

DESCRIPTION

Styptic Pencil

- Helps Stop Bleeding Quickly
- Great for Use on Nicks and Minor Cuts from Shaving